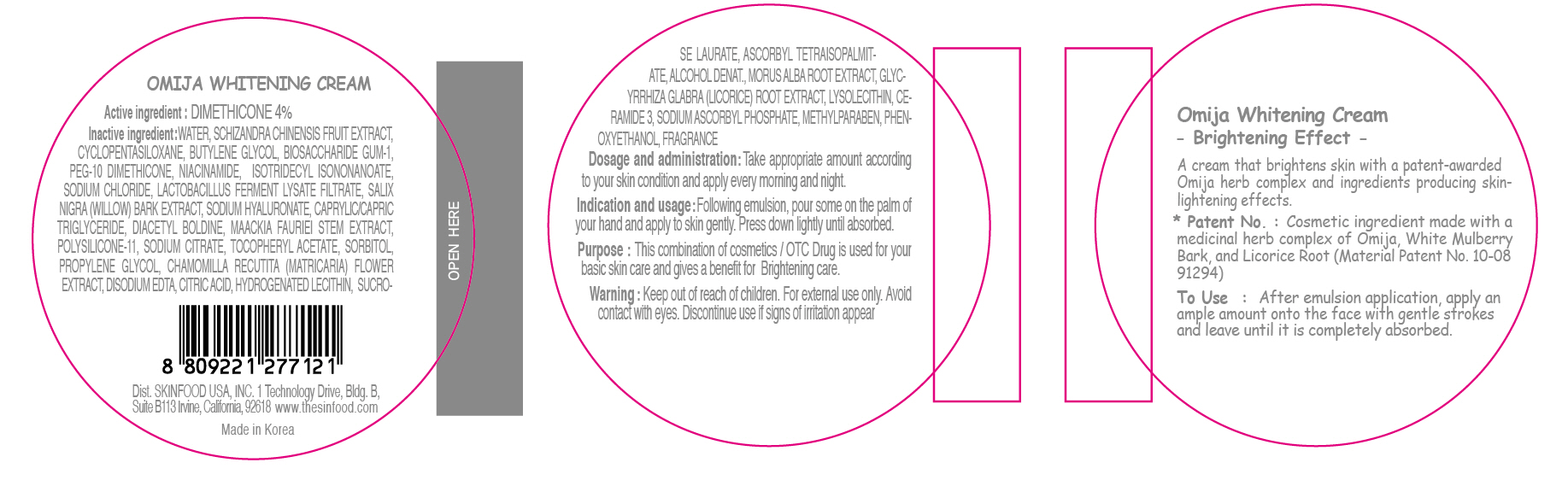 DRUG LABEL: OMIJA WHITENING
NDC: 76214-007 | Form: CREAM
Manufacturer: SKINFOOD CO., LTD.
Category: otc | Type: HUMAN OTC DRUG LABEL
Date: 20110722

ACTIVE INGREDIENTS: DIMETHICONE 2 g/50 g
INACTIVE INGREDIENTS: WATER; SCHISANDRA CHINENSIS FRUIT; CYCLOMETHICONE 5; BUTYLENE GLYCOL; BIOSACCHARIDE GUM-1; NIACINAMIDE; ISOTRIDECYL ISONONANOATE; SODIUM CHLORIDE; SALIX NIGRA BARK; METHYLPARABEN; PHENOXYETHANOL; MAACKIA FLORIBUNDA STEM; SODIUM CITRATE; SORBITOL; PROPYLENE GLYCOL; CHAMOMILE; EDETATE DISODIUM; HYDROGENATED SOYBEAN LECITHIN; SUCROSE LAURATE; MORUS ALBA ROOT; GLYCYRRHIZA GLABRA; CERAMIDE 3; SODIUM ASCORBYL PHOSPHATE

Drug Facts

Active ingredient: DIMETHICONE

Inactive ingredients:

WATER, SCHIZANDRA CHINENSIS FRUIT EXTRACT, CYCLOPENTASILOXANE, BUTYLENE GLYCOL, BIOSACCHARIDE GUM-1, PEG-10 DIMETHICONE, NIACINAMIDE, ISOTRIDECYL ISONONANOATE, SODIUM CHLORIDE, LACTOBACILLUS FERMENT LYSATE FILTRATE, SALIX NIGRA (WILLOW) BARK EXTRACT, SODIUM HYALURONATE, CAPRYLIC/CAPRIC TRIGLYCERIDE, DIACETYL BOLDINE, MAACKIA FAURIEI STEM EXTRACT, POLYSILICONE-11, SODIUM CITRATE, TOCOPHERYL ACETATE, SORBITOL, PROPYLENE GLYCOL, CHAMOMILLA RECUTITA (MATRICARIA) FLOWER EXTRACT, DISODIUM EDTA, CITRIC ACID, HYDROGENATED LECITHIN, SUCROSE LAURATE, ASCORBYL TETRAISOPALMITATE, ALCOHOL DENAT., MORUS ALBA ROOT EXTRACT, GLYCYRRHIZA GLABRA (LICORICE) ROOT EXTRACT, LYSOLECITHIN, CERAMIDE 3, SODIUM ASCORBYL PHOSPHATE, METHYLPARABEN, PHENOXYETHANOL, FRAGRANCE

Purpose:

This combination of cosmetics is used for your basic skin care and gives a benefit for Brightening care.

Warnings:

For external use only. Avoid contact with eyes. Discontinue use if signs of irritation appear.

Keep out of reach of children:

Keep out of reach of children.

Indication and usage:

Following emulsion, pour some on the palm of your hand and apply to skin gently. Press down lightly until absorbed.

Dosage and administration:

Take appropriate amount according to your skin condition and apply every morning and night.